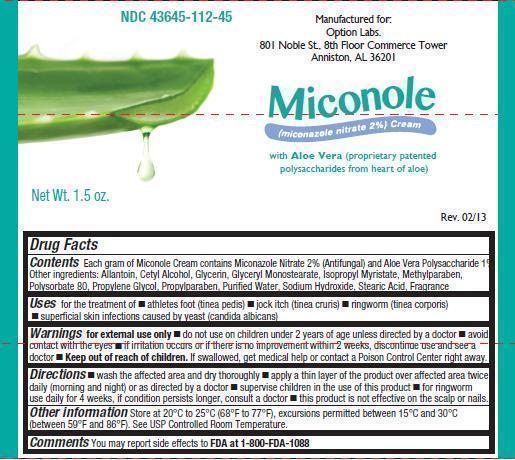 DRUG LABEL: Miconole
NDC: 43645-112 | Form: CREAM
Manufacturer: Option Labs
Category: otc | Type: HUMAN OTC DRUG LABEL
Date: 20130815

ACTIVE INGREDIENTS: MICONAZOLE NITRATE 20 mg/1 g
INACTIVE INGREDIENTS: ALOE VERA LEAF; ALLANTOIN; CETYL ALCOHOL; GLYCERIN; GLYCERYL MONOSTEARATE; ISOPROPYL MYRISTATE; METHYLPARABEN; POLYSORBATE 80; PROPYLENE GLYCOL; PROPYLPARABEN; WATER; SODIUM HYDROXIDE; STEARIC ACID

Miconole

Drug Facts

Miconazole Nitrate 2%

Aloe Vera Polysaccharide 1%

Purpose

Antifungal

Other ingredients:

Allantoin, Cetyl Alcohol, Glycerin, Glyceryl Monostearate, Isopropyl Myristate, Methylparaben, Polysorbate 80, Propylene Glycol, Propylparaben, Purified Water, Sodium Hydroxide, Stearic Acid, Fragrance

Uses

for the treatment of

- athletes foot (tinea pedis)
- jock itch (tinea cruris)
- ringworm (tinea corporis)
- superficial skin infections caused by yeast (candida albicans)

Warnings

for external use only

- do not use on children under 2 years of age unless directed by a doctor
- avoid contact with eyes
- If irritation occurs or if there is no improvement within 2 weeks, discontinue use and see a doctor

Keep out of reach of children.

If swallowed, get medical help or contact a Poison Control Center right away.

Directions

- wash the affected area and dry thoroughly
- apply a thin layer of the product over affected area twice daily (morning and night) or as directed by a doctor
- supervise children in the use of this product
- for ringworm use daily for 4 weeks, if condition persists longer, consult a doctor
- this product is not effective on the scalp or nails.

Other Information

Store at 20°C - 25°C (68°F - 77°F), excursions permitted between 15°C and 30°C (between 59°F and 86°F). See USP Controlled Room Temperature.

Comments

You may report side effects to FDA at 1-800-FDA-1088

PRINCIPAL DISPLAY PANEL

NDC 43645-112-45

Manufactured for:

Option Labs.

801 Noble St., 8th Floor Commerce Tower

Anniston, AL 36201

Miconole

(miconazole nitrate 2%) Cream

with Aloe Vera (proprietary patented

polysaccharides from heart of aloe)

Net Wt. 1.5 oz.

Rev. 02/13